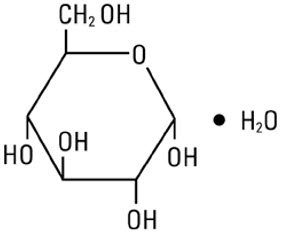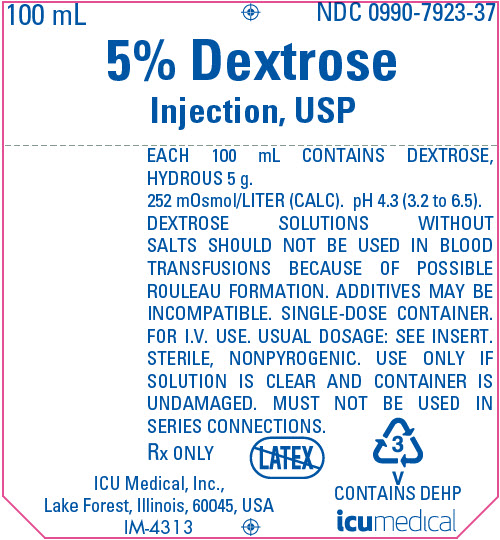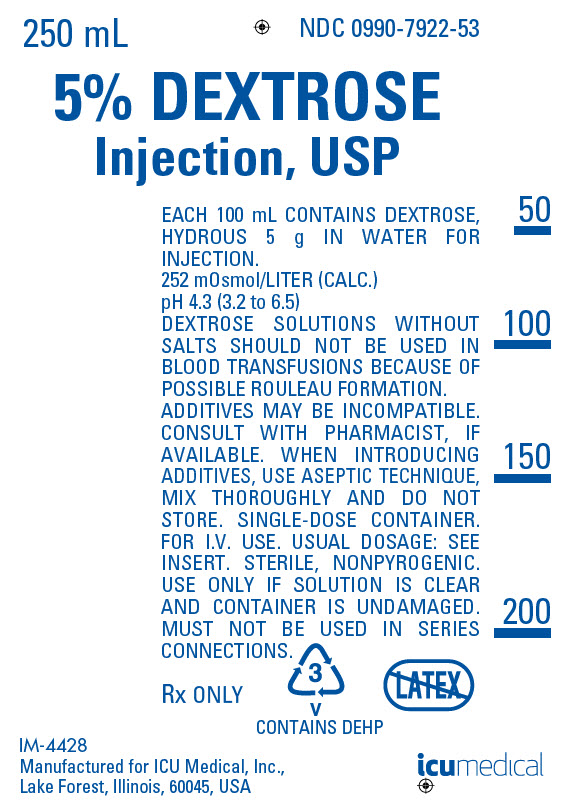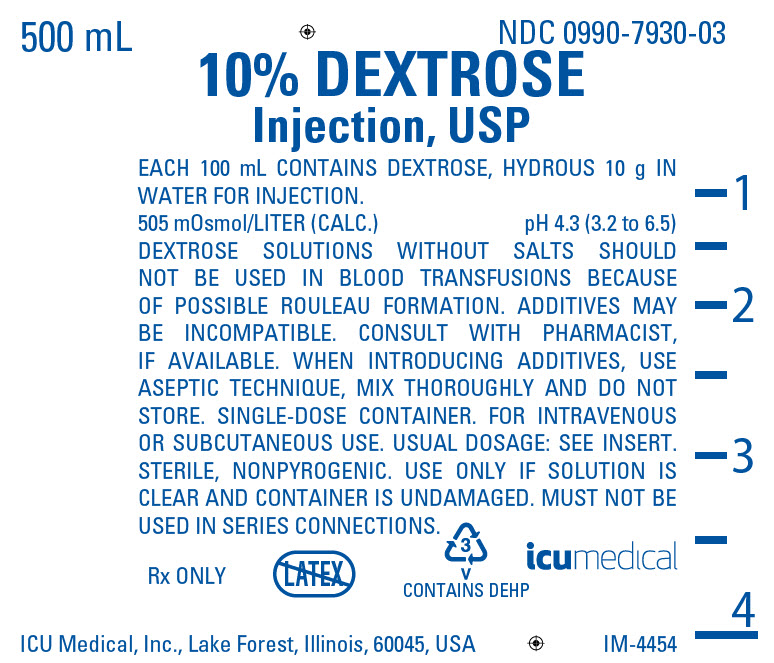 DRUG LABEL: Dextrose
NDC: 0990-7923 | Form: INJECTION, SOLUTION
Manufacturer: ICU Medical, Inc.
Category: prescription | Type: HUMAN PRESCRIPTION DRUG LABEL
Date: 20251102

ACTIVE INGREDIENTS: DEXTROSE MONOHYDRATE 5 g/100 mL
INACTIVE INGREDIENTS: WATER

HIGHLIGHTS OF PRESCRIBING INFORMATION

These highlights do not include all the information needed to use DEXTROSE INJECTION (5% and 10%) safely and effectively. See full prescribing information for DEXTROSE INJECTION (5% and 10%).
DEXTROSE Injection, for intravenous use
Initial U.S. Approval: 1940

RECENT MAJOR CHANGES

Dosage and Administration (2.1, 2.2, 2.3) | 06/2025
Contraindications (4) | 06/2025
Warnings and Precautions (5.1, 5.2, 5.3, 5.4, 5.5, 5.6, 5.7) | 06/2025

1 INDICATIONS AND USAGE

Dextrose Injection (5% and 10%) is indicated as a source of water and calories in adult and pediatric patients, and may also be used as a diluent for reconstitution of a powder or liquid drug product. (1)

2 DOSAGE AND ADMINISTRATION

- Only for intravenous infusion. (2.1)
- Infusion rate depends on the age, weight, clinical and metabolic conditions of the patient and concomitant therapy. See full prescribing information for more information on preparation, administration, and dosing considerations. (2.1, 2.2, 2.3)

3 DOSAGE FORMS AND STRENGTHS

Injection:

- 5% (5 g/100 mL) (50 mg/mL) of dextrose hydrous in single-dose flexible containers: 25 mL, 50 mL, 100 mL, 150 mL, 250 mL, 500 mL, and 1000 mL. (3)
- 10% (10 g/100 mL) (100 mg/mL) of dextrose hydrous in single-dose flexible containers: 250 mL, 500 mL, and 1000 mL. (3)

4 CONTRAINDICATIONS

- Clinically significant hyperglycemia. (4)
- Known hypersensitivity to dextrose. (4)

5 WARNINGS AND PRECAUTIONS

- Neonatal Hypoglycemia: Closely monitor blood glucose concentrations to ensure adequate glycemic control. (5.1)
- Hyperglycemia and Hyperosmolar Hyperglycemic State: Use with caution in patients with known subclinical or overt diabetes mellitus. (5.2)
- Hypersensitivity Reactions: Monitor for signs and symptoms and discontinue infusion immediately if reaction occurs. (5.3)
- Phlebitis and Thrombosis: Remove catheter as soon as possible if thrombophlebitis develops. (2.1, 5.4)
- Hyponatremia: Monitor serum sodium and chloride concentrations, fluid status, acid-base balance, and neurologic status. (5.5)
- Electrolyte Imbalance and Fluid Overload: Monitor changes in fluid balance, electrolyte concentrations, and acid-base balance during administration. (5.6)
- Refeeding Syndrome: Monitor laboratory parameters. (5.7)

6 ADVERSE REACTIONS

The most common adverse reactions are hyperglycemia, hypersensitivity reactions, hyponatremia, infection, both systemic and at the injection site, vein thrombosis or phlebitis, and electrolyte imbalance. (6)

To report SUSPECTED ADVERSE REACTIONS, contact ICU Medical, Inc. at 1-800-441-4100 or FDA at 1-800-FDA-1088 or www.fda.gov/medwatch.

7 DRUG INTERACTIONS

Drugs with Effects on Glycemic Control and Electrolyte Balance: Monitor blood glucose concentrations, fluid balance, serum electrolyte concentrations, and acid-base balance. Avoid use of Dextrose Injection in patients receiving drugs associated with hyponatremia. (7.1)

8 USE IN SPECIFIC POPULATIONS

Pediatric Use: Increased risk of hypoglycemia/hyperglycemia and imbalances in fluid/electrolytes; monitor serum glucose concentrations, volume status, and electrolytes. (8.4)

FULL PRESCRIBING INFORMATION

1 INDICATIONS AND USAGE

Dextrose Injection (5% and 10%) is indicated as a source of water and calories in adult and pediatric patients, and may also be used as a diluent for reconstitution of a powder or liquid drug product.

2 DOSAGE AND ADMINISTRATION

2.1 Important Administration Instructions

Dextrose Injection (5% and 10%) is intended for intravenous use.

- Use a peripheral vein to administer if the final dextrose concentration is 5% or less and the osmolarity is less than 900 mOsm/L.
- Consider using a central vein to administer hypertonic solutions with osmolarity of 900 mOsm/L or greater to avoid venous irritation [see Warnings and Precautions (5.3)].
- Do not administer Dextrose Injection (5% and 10%) simultaneously with blood products through the same administration set because of the possibility of pseudoagglutination or hemolysis.
- Use of a final filter is recommended during administration of parenteral solutions, where possible.
- Discard the unused portion.
- Avoid use with chemotherapy agents. Consult the specific chemotherapy agent prescribing information to determine the appropriate diluent.

2.2 Important Preparation Information

Visually inspect the Dextrose Injection (5% and 10%) for particulate matter and discoloration. Do not administer Dextrose Injection (5% and 10%) if the solution is cloudy, there are precipitates, or the container is damaged.

To reduce the risk of air embolism, adhere to the following preparation instructions for Dextrose Injection (5% and 10%):

- Use a non-vented infusion set or close the vent on a vented set.
- Use a dedicated line without any connections (do not connect flexible containers in series).
- Do not pressurize the flexible container to increase flow rates.
- If using a pumping device to administer Dextrose Injection (5% and 10%), turn off the pump before the container is empty.

To Open:

Tear outer wrap at notch and remove solution container. If supplemental medication is desired, follow directions below before preparing for administration.

To Add Medication:

1. Prepare additive port.
2. Using aseptic technique and an additive delivery needle of appropriate length, puncture resealable additive port at target area, inner diaphragm and inject. Withdraw needle after injecting medication.
3. The additive port may be protected by covering with an additive cap.
4. Mix container contents thoroughly.

Preparation for Administration

(Use aseptic technique)

1. Close flow control clamp of administration set.
2. Remove cover from outlet port at bottom of container.
3. Insert piercing pin of administration set into port with a twisting motion until the set is firmly seated. NOTE: When using a vented administration set, replace bacterial retentive air filter with piercing pin cover. Insert piercing pin with twisting motion until shoulder of air filter housing rests against the outlet port flange.
4. Suspend container from hanger.
5. Squeeze and release drip chamber to establish proper fluid level in chamber.
6. Attach venipuncture device to set.
7. Open clamp to expel air from set and venipuncture device. Close clamp.
8. Perform venipuncture.
9. Regulate rate of administration with flow control clamp.

2.3 Dosage Considerations

The choice of dextrose concentration, rate, and volume depends on the age, weight, clinical and metabolic conditions of the patient and concomitant therapy.

Dextrose Injection (5% and 10%) administration rate should be based on the patient's tolerance of dextrose, especially for premature infants with low birth weight.

Increase the infusion rate gradually as needed; frequently monitor blood glucose concentrations to avoid hyperglycemia [see Warnings and Precautions (5.2), Use in Specific Populations (8.4)].

3 DOSAGE FORMS AND STRENGTHS

Injection:

- 5% (5 g/100 mL) (50 mg/mL) of dextrose hydrous in a clear, sterile, and nonpyrogenic solution in single-dose flexible containers: 25 mL, 50 mL, 100 mL, 150 mL, 250 mL, 500 mL, and 1000 mL
- 10% (10 g/100 mL) (100 mg/mL) of dextrose hydrous in a clear, sterile, and nonpyrogenic solution in single-dose flexible containers: 250 mL, 500 mL, and 1000 mL

4 CONTRAINDICATIONS

Dextrose Injection (5% and 10%) is contraindicated in patients with:

- Clinically significant hyperglycemia [see Warnings and Precautions (5.2)].
- Known hypersensitivity to dextrose [see Warnings and Precautions (5.3)].

5 WARNINGS AND PRECAUTIONS

5.1 Neonatal Hypoglycemia

Neonates, especially preterm neonates with low birth weight, are at increased risk of developing hypoglycemia. Closely monitor blood glucose concentration during treatment with Dextrose Injection (5% and 10%) to ensure adequate glycemic control in order to avoid potential long-term adverse effects.

5.2 Hyperglycemia and Hyperosmolar Hyperglycemic State

The use of Dextrose Injection (5% and 10%) in patients with impaired glucose tolerance may worsen hyperglycemia. Administration of dextrose at a rate exceeding the patient's utilization rate may lead to hyperglycemia, coma, and death.

Hyperglycemia is associated with an increase in serum osmolality, resulting in osmotic diuresis, dehydration and electrolyte losses [see Warnings and Precautions (5.6), Use in Specific Populations (8.4)]. Patients with underlying CNS disease and renal impairment who receive dextrose infusions may be at greater risk of developing hyperosmolar hyperglycemic state.

Monitor blood glucose levels and treat hyperglycemia to maintain levels within normal limits while administering Dextrose Injection (5% and 10%). Insulin may be administered or adjusted to maintain optimal blood glucose levels during Dextrose Injection (5% and 10%) administration.

5.3 Hypersensitivity Reactions

Hypersensitivity reactions, including anaphylaxis, have been reported with Dextrose Injection (5% and 10%) administration [see Adverse Reactions (6)]. Stop administration of Dextrose Injection (5% and 10%) immediately if signs or symptoms of a hypersensitivity reaction develop. Initiate appropriate treatment as clinically indicated.

5.4 Phlebitis and Thrombosis

The infusion of hypertonic solutions into a peripheral vein may result in vein irritation, vein damage, and/or thrombosis [see Dosage and Administration (2.1)]. If thrombophlebitis develops, remove the catheter as soon as possible.

5.5 Hyponatremia

Dextrose Injection (5% and 10%) may cause hyponatremia. Hyponatremia can lead to acute hyponatremic encephalopathy characterized by headache, nausea, seizures, lethargy, and vomiting. The risk of hospital-acquired hyponatremia is increased in younger pediatric patients, geriatric patients, patients treated with diuretics, and patients with cardiac or pulmonary failure or with the syndrome of inappropriate antidiuretic hormone (SIADH) (e.g., postoperative patients, patients concomitantly treated with arginine vasopressin analogs or certain antiepileptic, psychotropic, and cytotoxic drugs) [see Drug Interactions (7.1), Use in Specific Populations (8.4)].

Avoid Dextrose Injection (5% and 10%) in patients with or at risk for hyponatremia. If use cannot be avoided, closely monitor serum sodium concentrations, chloride concentrations, fluid status, acid-base balance, and neurologic status [see Warnings and Precautions (5.6)].

5.6 Electrolyte Imbalance and Fluid Overload

Electrolyte deficits, particularly serum potassium and phosphate, may occur during prolonged use of Dextrose Injection (5% and 10%).

Depending on the administered volume and the infusion rate, Dextrose Injection (5% and 10%) can cause fluid overload, including pulmonary edema.

Avoid Dextrose Injection (5% and 10%) in patients at risk for fluid and/or solute overload. If use cannot be avoided in these patients, monitor fluid balance, electrolyte concentrations, and acid-base balance, especially during prolonged use. Additional monitoring is recommended for patients with water and electrolyte disturbances that could be aggravated by increased glucose, insulin administration and/or free water load.

5.7 Refeeding Syndrome

Refeeding severely undernourished patients may result in refeeding syndrome, characterized by the intracellular shift of potassium, phosphorus, and magnesium as the patient becomes anabolic. Thiamine deficiency and fluid retention may also develop. To prevent these complications, monitor severely undernourished patients and slowly increase nutrient intake.

6 ADVERSE REACTIONS

The following clinically significant adverse reactions are described elsewhere in the labeling:

- Neonatal Hypoglycemia [see Warnings and Precautions (5.1)]
- Hyperglycemia and Hyperosmolar Hyperglycemic State [see Warnings and Precautions (5.2)]
- Hypersensitivity Reactions [see Warnings and Precautions (5.3)]
- Phlebitis and Thrombosis [see Warnings and Precautions (5.4)]
- Hyponatremia [see Warnings and Precautions (5.5)]
- Electrolyte Imbalance and Fluid Overload [see Warnings and Precautions (5.6)]
- Refeeding syndrome [see Warnings and Precautions (5.7)]

The following adverse reactions associated with the use of Dextrose Injection (5% and 10%) were identified in clinical studies or postmarketing reports. Because some of these reactions were reported voluntarily from a population of uncertain size, it is not possible to reliably estimate their frequency or establish a causal relationship to drug exposure.

Administration site conditions: blister, erythema, extravasation, pain, phlebitis, vein damage, thrombosis

Immune system disorders: anaphylaxis, angioedema, bronchospasm, chills, hypotension, pruritis, pyrexia, rash

Cardiovascular disorders: cyanosis, volume overload

7 DRUG INTERACTIONS

7.1 Drugs with Effects on Glycemic Control and Electrolyte Balance

Dextrose Injection (5% and 10%) can affect glycemic control, vasopressin, and fluid and/or electrolyte balance [see Warnings and Precautions (5.1, 5.2, 5.4, 5.5)]. Monitor patients' blood glucose concentrations, fluid balance, serum electrolyte concentrations, and acid-base balance.

Concomitant administration of Dextrose Injection (5% and 10%) with drugs associated with hyponatremia may increase the risk of developing hyponatremia. Drugs associated with hyponatremia include diuretics and those that cause SIADH (e.g., selective serotonin reuptake inhibitors (SSRIs), serotonin and norepinephrine reuptake inhibitors (SNRIs), arginine vasopressin analogs, certain antiepileptic, psychotropic, and cytotoxic drugs). Avoid use of Dextrose Injection (5% and 10%) in patients receiving drugs associated with hyponatremia. If use cannot be avoided, closely monitor serum sodium concentrations during concomitant use [see Warnings and Precautions (5.5)].

8 USE IN SPECIFIC POPULATIONS

8.1 Pregnancy

Risk Summary

Dextrose Injection (5% and 10%) has been used for decades during labor and delivery. Although there are a few case reports that describe adverse effects of dextrose use in other stages of pregnancy, exposure during pregnancy in general is not expected to cause major birth defects, miscarriage, or adverse maternal or fetal outcomes. Animal reproduction studies have not been conducted with dextrose.

The background risk of major birth defects and miscarriage for the indicated population is unknown. All pregnancies have a background risk of birth defect, loss, or other adverse outcomes. In the U.S. general population, the estimated background risk of major birth defects and miscarriage in clinically recognized pregnancies is 2 to 4% and 15 to 20%, respectively.

8.2 Lactation

Risk Summary

Dextrose Injection (5% and 10%) has been used for decades and is not expected to cause harm to a breastfed infant. There are no data on the effects of Dextrose Injection (5% and 10%) on levels of glucose in human milk, on the breastfed infant, or on milk production. The developmental and health benefits of breastfeeding should be considered along with the mother's clinical need for Dextrose Injection (5% and 10%) and any potential adverse effects on the breastfed infant from Dextrose Injection (5% and 10%) or from the underlying maternal condition.

8.4 Pediatric Use

Dextrose Injection (5% and 10%) is indicated in pediatric patients as a source of water and calories, and may also be used as a diluent for reconstitution of a powder or liquid drug product.

Neonates, especially premature infants with low birth weight, are at increased risk of developing hypo-or hyperglycemia. Therefore, they need close monitoring during treatment with intravenous glucose infusions to ensure adequate glycemic control in order to avoid potential long-term adverse effects.

Dextrose Injection (5% and 10%) can cause imbalances in fluid and electrolytes in pediatric patients and requires close monitoring of volume status and plasma electrolyte concentrations, particularly in pediatric patients who may have impaired ability to regulate fluids and electrolytes. Pediatric patients are at increased risk for developing hyponatremic encephalopathy [see Warnings and Precautions (5.5, 5.6)].

In very low birth weight neonates, excessive or rapid administration of Dextrose Injection (5% and 10%) may result in increased serum osmolality and risk of intracerebral hemorrhage.

8.5 Geriatric Use

Dextrose Injection (5% and 10%) has not been studied in sufficient number of patients aged 65 and over to determine whether they respond differently from younger patients. Geriatric patients are at increased risk of developing hyponatremia and hyponatremic encephalopathy [see Warnings and Precautions (5.5)]. Other reported clinical experience has not identified differences in responses between the geriatric and younger adult patients. In general, the infusion rate for geriatric patients should start slow and be titrated up cautiously, reflecting their greater risk for electrolyte abnormalities and fluid overload.

Dextrose is known to be substantially excreted by the kidney, and the risk of adverse reactions to Dextrose Injection (5% and 10%) may be greater in patients with impaired renal function. Because geriatric patients are more likely to have impaired renal function, care should be taken in selection of infusion rate and patients should be closely monitored during Dextrose Injection (5% and 10%) treatment.

10 OVERDOSAGE

A medication error resulting in a high infusion rate of Dextrose Injection (5% and 10%) can cause hyperglycemia, hyperosmolality, and adverse effects on fluid and electrolyte balance [see Warnings and Precautions (5.2, 5.6)].

Severe hyperglycemia and severe dilutional hyponatremia, and their complications, can be fatal. In the event of overdosage (overhydration or solute overload) during Dextrose Injection (5% and 10%) treatment, discontinue the infusion. Institute corrective measures such as administration of exogenous insulin, and treat adverse effects on the CNS, respiratory, and cardiovascular systems [see Warnings and Precautions (5.2, 5.6)].

11 DESCRIPTION

Dextrose, USP is chemically designated D-glucose monohydrate (C6H12O6 ∙ H2O), a hexose sugar freely soluble in water.

The molecular weight of dextrose (D-glucose) monohydrate is 198.17. It has the following structural formula:

Water for Injection, USP is chemically designated H2O.

Dextrose Injection, USP (5% and 10%) solutions are sterile and nonpyrogenic. They are parenteral solutions containing various concentrations of dextrose in water for injection intended for intravenous administration.

Each 100 mL of 5% Dextrose Injection, USP, contains dextrose, hydrous 5 g in water for injection. The caloric value is 170 kcal/L. The osmolarity is 252 mOsmol/L (calc.), which is slightly hypotonic.

Each 100 mL of 10% Dextrose Injection, USP, contains dextrose, hydrous 10 g in water for injection. The caloric value is 340 kcal/L. The osmolarity is 505 mOsmol/L (calc.), which is hypertonic.

The pH for both concentrations is 4.3 (range is 3.2 to 6.5).

The solutions contain no bacteriostatic, antimicrobial agent or added buffer and each is supplied as single-dose containers.

Dextrose is derived from corn.

Exposure to temperatures above 25°C/77°F during transport and storage will lead to minor losses in moisture content. Higher temperatures lead to greater losses. It is unlikely that these minor losses will lead to clinically significant changes within the expiration period.

12 CLINICAL PHARMACOLOGY

12.1 Mechanism of Action

Dextrose provides a source of carbohydrate calories and is used to supplement nutrition by providing glucose parenterally.

12.2 Pharmacodynamics

The exposure-response relationship and time course of pharmacodynamic response for the safety and effectiveness of dextrose have not been fully characterized.

12.3 Pharmacokinetics

Dextrose is oxidized to carbon dioxide and water.

13 NONCLINICAL TOXICOLOGY

13.1 Carcinogenesis, Mutagenesis, Impairment of Fertility

Studies with dextrose to evaluate the drug's carcinogenic potential, mutagenic potential, or effects on fertility have not been performed.

16 HOW SUPPLIED/STORAGE AND HANDLING

Dextrose Injection, USP (5% and 10%) is a clear, sterile, nonpyrogenic solution of dextrose supplied in single-dose flexible plastic containers as shown in the accompanying Table.

NDC No. | Product | Container size (mL)
0990-7922-61 [Manufactured by ICU Medical, Inc., Lake Forest, Illinois, 60045, USA] | 5% Dextrose Injection, USP (5 g / 100 mL (50 mg/mL)) | 150
0990-7922-53 [Manufactured for ICU Medical, Inc., Lake Forest, Illinois, 60045, USA] | 5% Dextrose Injection, USP (5 g / 100 mL (50 mg/mL)) | 250
0990-7922-02 | 5% Dextrose Injection, USP (5 g / 100 mL (50 mg/mL)) | 250
0990-7922-03, | 5% Dextrose Injection, USP (5 g / 100 mL (50 mg/mL)) | 500
0990-7922-55, | 5% Dextrose Injection, USP (5 g / 100 mL (50 mg/mL)) | 500
0990-7922-09, | 5% Dextrose Injection, USP (5 g / 100 mL (50 mg/mL)) | 1000
0990-7923-20 | 5% Dextrose Injection, USP (5 g / 100 mL (50 mg/mL)) | 25
0990-7923-36 | 5% Dextrose Injection, USP (5 g / 100 mL (50 mg/mL)) | 50
0990-7923-13 | 5% Dextrose Injection, USP (5 g / 100 mL (50 mg/mL)) | 50
0990-7923-23 | 5% Dextrose Injection, USP (5 g / 100 mL (50 mg/mL)) | 100
0990-7923-37 | 5% Dextrose Injection, USP (5 g / 100 mL (50 mg/mL)) | 100
0990-7930-02 | 10% Dextrose Injection, USP (10 g / 100 mL (100 mg/mL)) | 250
0990-7930-03, | 10% Dextrose Injection, USP (10 g / 100 mL (100 mg/mL)) | 500
0990-7930-09, | 10% Dextrose Injection, USP (10 g / 100 mL (100 mg/mL)) | 1000

Storage and Handling

Store at 20°C to 25°C (68°F to 77°F); excursions permitted between 15°C to 30°C (59°F to 86°F) [See USP Controlled Room Temperature].

Protect from freezing.

IFU0000541

icumedical

PRINCIPAL DISPLAY PANEL - 100 mL Bag Label

100 mL
NDC 0990-7923-37

5% Dextrose
Injection, USP

EACH 100 mL CONTAINS DEXTROSE,
HYDROUS 5 g.
252 mOsmol/LITER (CALC). pH 4.3 (3.2 to 6.5).
DEXTROSE SOLUTIONS WITHOUT
SALTS SHOULD NOT BE USED IN BLOOD
TRANSFUSIONS BECAUSE OF POSSIBLE
ROULEAU FORMATION. ADDITIVES MAY BE
INCOMPATIBLE. SINGLE-DOSE CONTAINER.
FOR I.V. USE. USUAL DOSAGE: SEE INSERT.
STERILE, NONPYROGENIC. USE ONLY IF
SOLUTION IS CLEAR AND CONTAINER IS
UNDAMAGED. MUST NOT BE USED IN
SERIES CONNECTIONS.

Rx ONLY

ICU Medical, Inc.,
Lake Forest, Illinois, 60045, USA
IM-4313

3
V
CONTAINS DEHP

icumedical

PRINCIPAL DISPLAY PANEL - 250 mL Bag Label

250 mL
NDC 0990-7922-53

5% DEXTROSE
Injection, USP

EACH 100 mL CONTAINS DEXTROSE,
HYDROUS 5 g IN WATER FOR
INJECTION.
252 mOsmol/LITER (CALC.)
pH 4.3 (3.2 to 6.5)
DEXTROSE SOLUTIONS WITHOUT
SALTS SHOULD NOT BE USED IN
BLOOD TRANSFUSIONS BECAUSE OF
POSSIBLE ROULEAU FORMATION.
ADDITIVES MAY BE INCOMPATIBLE.
CONSULT WITH PHARMACIST, IF
AVAILABLE. WHEN INTRODUCING
ADDITIVES, USE ASEPTIC TECHNIQUE,
MIX THOROUGHLY AND DO NOT
STORE. SINGLE-DOSE CONTAINER.
FOR I.V. USE. USUAL DOSAGE: SEE
INSERT. STERILE, NONPYROGENIC.
USE ONLY IF SOLUTION IS CLEAR
AND CONTAINER IS UNDAMAGED.
MUST NOT BE USED IN SERIES
CONNECTIONS.

Rx ONLY

3
V
CONTAINS DEHP

IM-4428
Manufactured for ICU Medical, Inc.,
Lake Forest, Illinois, 60045, USA

icumedical

PRINCIPAL DISPLAY PANEL - 500 mL Bag Label

500 mL
NDC 0990-7930-03

10% DEXTROSE
Injection, USP

EACH 100 mL CONTAINS DEXTROSE, HYDROUS 10 g IN
WATER FOR INJECTION.
505 mOsmol/LITER (CALC.)
pH 4.3 (3.2 to 6.5)
DEXTROSE SOLUTIONS WITHOUT SALTS SHOULD
NOT BE USED IN BLOOD TRANSFUSIONS BECAUSE
OF POSSIBLE ROULEAU FORMATION. ADDITIVES MAY
BE INCOMPATIBLE. CONSULT WITH PHARMACIST,
IF AVAILABLE. WHEN INTRODUCING ADDITIVES, USE
ASEPTIC TECHNIQUE, MIX THOROUGHLY AND DO NOT
STORE. SINGLE-DOSE CONTAINER. FOR INTRAVENOUS
OR SUBCUTANEOUS USE. USUAL DOSAGE: SEE INSERT.
STERILE, NONPYROGENIC. USE ONLY IF SOLUTION IS
CLEAR AND CONTAINER IS UNDAMAGED. MUST NOT BE
USED IN SERIES CONNECTIONS.

Rx ONLY

3
V
CONTAINS DEHP

icumedical

ICU Medical, Inc., Lake Forest, Illinois, 60045, USA
IM-4454